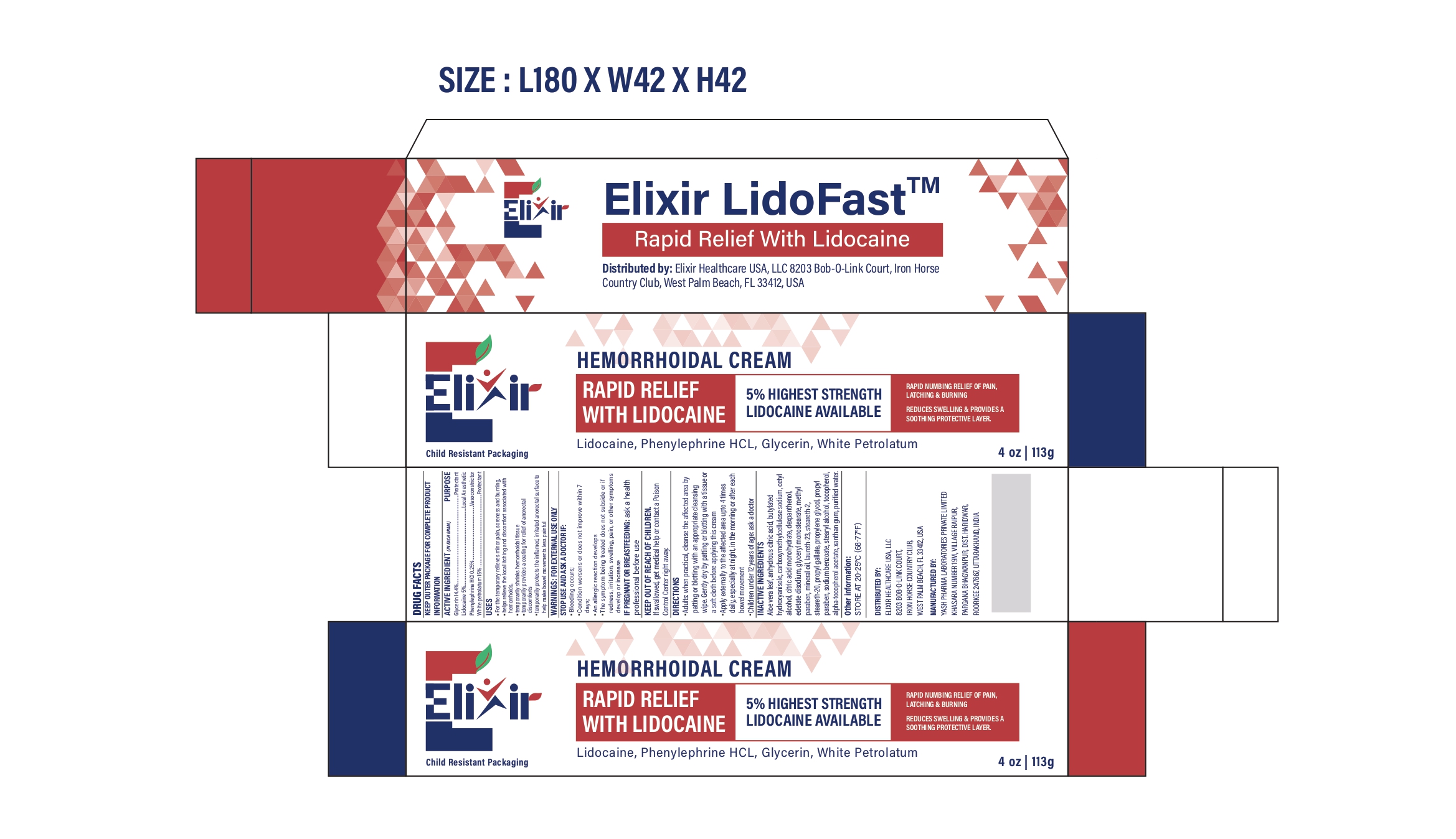 DRUG LABEL: ElixirLidoFast Rapid Relief
NDC: 84546-0006 | Form: CREAM
Manufacturer: ELIXIR HEALTHCARE USA, LLC.
Category: otc | Type: HUMAN OTC DRUG LABEL
Date: 20251213

ACTIVE INGREDIENTS: PETROLATUM 150 mg/1 g; PHENYLEPHRINE HYDROCHLORIDE 2.5 mg/1 g; GLYCERIN 144 mg/1 g; LIDOCAINE 50 mg/1 g
INACTIVE INGREDIENTS: BUTYLATED HYDROXYANISOLE; CARBOXYMETHYLCELLULOSE SODIUM, UNSPECIFIED; CETYL ALCOHOL; CITRIC ACID MONOHYDRATE; DEXPANTHENOL; EDETATE DISODIUM; GLYCERYL MONOSTEARATE; METHYLPARABEN; MINERAL OIL; LAURETH-23; STEARETH-2; STEARETH-20; PROPYL GALLATE; PROPYLENE GLYCOL; PROPYLPARABEN; WATER; SODIUM BENZOATE; STEARYL ALCOHOL; TOCOPHEROL; .ALPHA.-TOCOPHEROL ACETATE; XANTHAN GUM; ALOE VERA LEAF; ANHYDROUS CITRIC ACID

ElixirLidoFast Drug Facts

Active Ingredients

Glycerin 14.4%

Lidocaine 5%

Phenylephrine HCl 0.25%

White petrolatum 15%

Purposes

Protectant

Local anesthetic

Vasoconstrictor

Protectant

Uses

- for temporary relief of pain, soreness and burning
- helps relieve the local itching and discomfort associated with hemorrhoids
- temporarily shrinks hemorrhoidal tissue
- temporarily provides a coating for relief of anorectal discomforts
- temporarily protects the inflamed irritated anorectal surface to help make bowel movements less painful

Warnings

For external use only

Ask a doctor before use if you have heart disease high blood pressure thyroid disease diabetes difficulty in urination due to enlargement of the prostate gland

Ask a doctor or pharmacist before use if you arepresently taking a prescription drug for high blood pressure or depression.

When using this product

- do not exceed the recommended daily dosage unless directed by a doctor
- do not put into the rectum by using fingers or any mechanical device or applicator

Stop use and ask a doctor if

- bleeding occurs
- condition worsens or does not improve within 7 days
- an allergic reaction develops
- the symptom being treated does not subside or if redness, irritation, swelling, pain, or other symptoms develop or increase

PREGNANCY OR BREAST FEEDING

If pregnant or breast-feeding,ask a health professional before use.

Keep out of reach of children.If swallowed, get medical help or contact a Poison Control Center right away.

Directions

- adults: when practical, cleanse the affected area by patting or blotting with an appropriate cleansing wipe. Gently dry by patting or blotting with a tissue or a soft cloth before applying this cream.
- apply externally to the affected area up to 4 times daily, especially at night, in the morning or after each bowel movement
- children under 12 years of age: ask a doctor

Other information

store at 20-25°C (68-77°F)

Inactive ingredients

Aloe vera leaf, anhydrous citric acid, butylated hydroxyanisole, carboxymethylcellulose sodium, cetyl alcohol, citric acid monohydrate, dexpanthenol, edetate disodium, glyceryl monostearate, methyl paraben, mineral oil, laureth 23, steareth 2, steareth 20, propyl gallate, propylene glycol, propyl paraben, sodium benzoate, stearyl alcohol, tocopherol, alpha-tocopherol acetate, xanthan gum, purified water.

PRINCIPAL DISPLAY PANEL

TO OPEN PUSH DOWN ON CAP WHILE

TURNING COUNTERCLOCKWISE

Elixir

HEMORRHOIDAL CREAM

RAPID RELIEF WITH LIDOCAINE, 5% HIGHEST STRENGTH LIDOCAINE AVAILABLE

RAPID NUMBING RELIEF OF PAIN, LATCHING & BURNING

REDUCES SWELLING & PROVIDES A SOOTHING PROTECTIVE LAYER.

Lidocaine, Phenylephrine HCL, Glycerin, White Petrolatum

4 oz|113g

Child Resistant Packaging